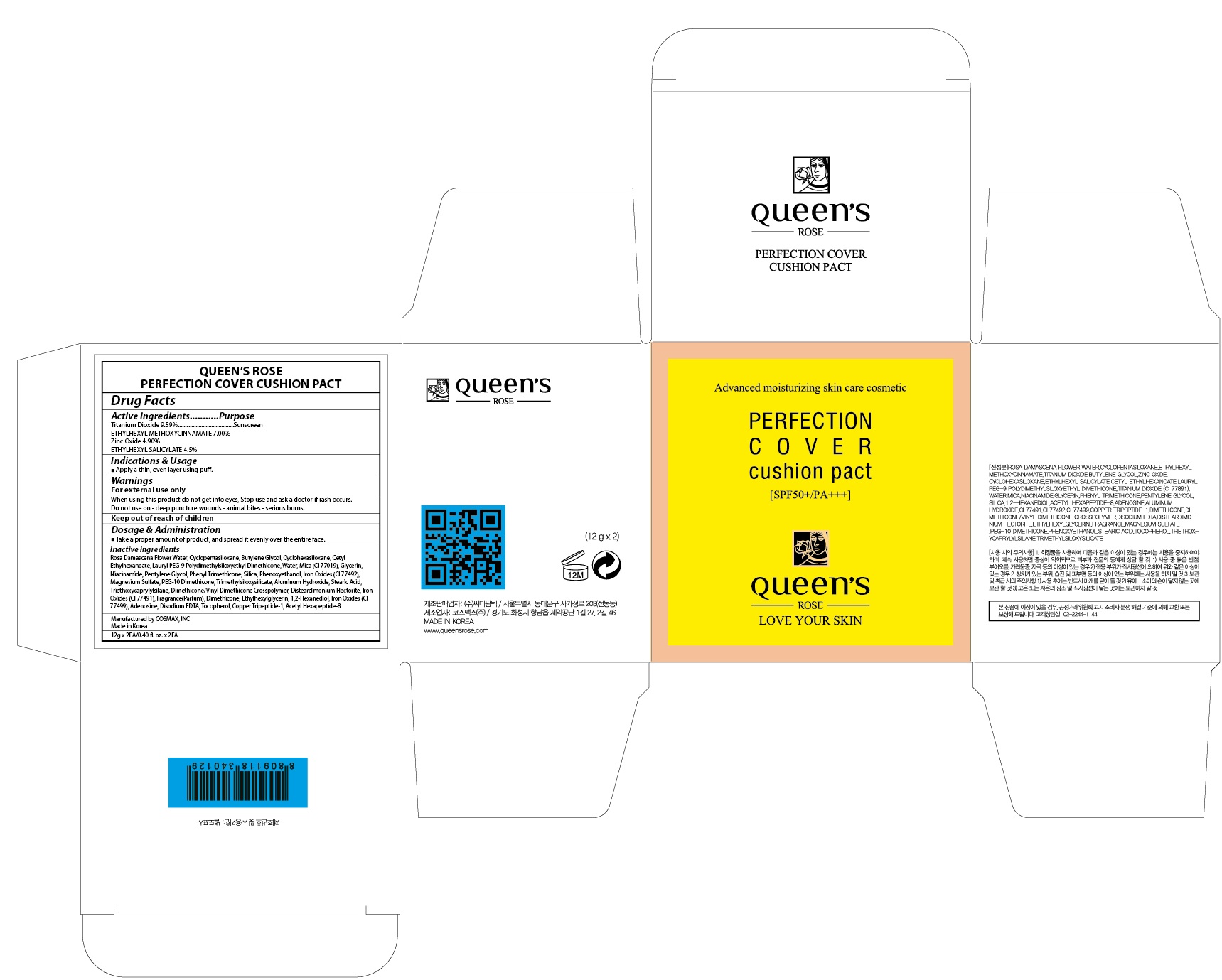 DRUG LABEL: QUEENS ROSE PERFECTION COVER CUSHION PACT
NDC: 71252-120 | Form: POWDER
Manufacturer: Cdpharmtec Co.,ltd
Category: otc | Type: HUMAN OTC DRUG LABEL
Date: 20170324

ACTIVE INGREDIENTS: Titanium Dioxide 1.15 g/12 g; Octinoxate 0.84 g/12 g; Zinc Oxide 0.58 g/12 g; Octisalate 0.54 g/12 g
INACTIVE INGREDIENTS: ROSA DAMASCENA FLOWER OIL; Butylene Glycol

ACTIVE INGREDIENT

Active ingredients: Titanium Dioxide 9.59%, ETHYLHEXYL METHOXYCINNAMATE 7.00%, Zinc Oxide 4.90%, ETHYLHEXYL SALICYLATE 4.5%

INACTIVE INGREDIENT

Inactive ingredients: Rosa Damascena Flower Water, Cyclopentasiloxane, Butylene Glycol, Cyclohexasiloxane, Cetyl Ethylhexanoate, Lauryl PEG-9 Polydimethylsiloxyethyl Dimethicone, Water, Mica (CI 77019), Glycerin, Niacinamide, Pentylene Glycol, Phenyl Trimethicone, Silica, Phenoxyethanol, Iron Oxides (CI 77492), Magnesium Sulfate, PEG-10 Dimethicone, Trimethylsiloxysilicate, Aluminum Hydroxide, Stearic Acid, Triethoxycaprylylsilane, Dimethicone/Vinyl Dimethicone Crosspolymer, Disteardimonium Hectorite, Iron Oxides (CI 77491), Fragrance(Parfum), Dimethicone, Ethylhexylglycerin, 1,2-Hexanediol, Iron Oxides (CI 77499), Adenosine, Disodium EDTA, Tocopherol, Copper Tripeptide-1, Acetyl Hexapeptide-8

PURPOSE

Purpose: Sunscreen

WARNINGS

Warnings: For external use only When using this product do not get into eyes, Stop use and ask a doctor if rash occurs. Do not use on - deep puncture wounds - animal bites - serious burns.

Keep out of reach of children

DESCRIPTION

Indications & Usage: Apply a thin, even layer using puff.

Dosage & Administration: Take a proper amount of product, and spread it evenly over the entire face..